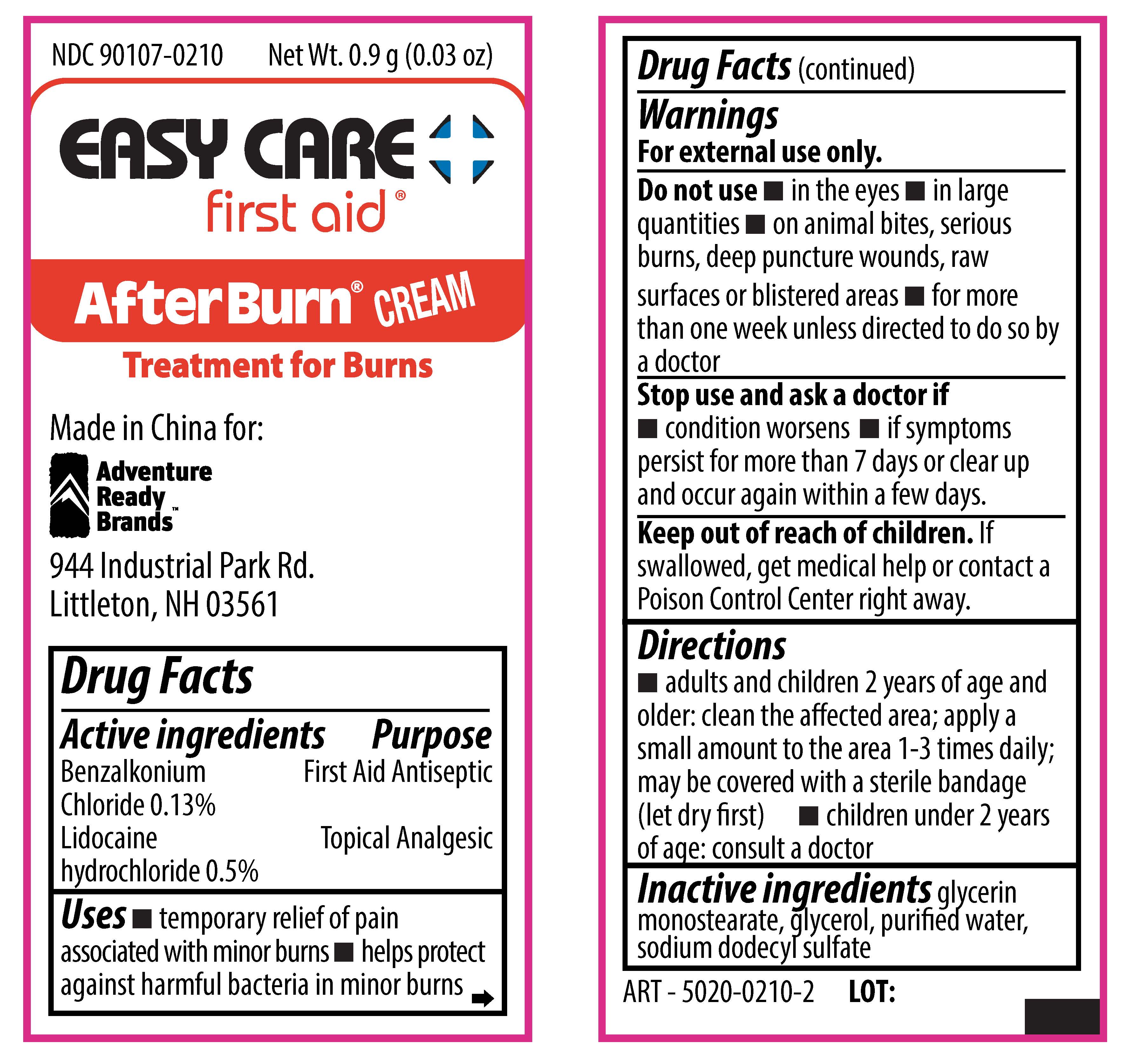 DRUG LABEL: Easy Care First Aid AfterBurn
NDC: 90107-0210 | Form: CREAM
Manufacturer: Adventure Ready Brands
Category: otc | Type: HUMAN OTC DRUG LABEL
Date: 20201210

ACTIVE INGREDIENTS: BENZALKONIUM CHLORIDE 0.13 g/100 g; LIDOCAINE HYDROCHLORIDE 0.5 g/100 g
INACTIVE INGREDIENTS: SODIUM LAURYL SULFATE; GLYCERYL MONOSTEARATE; GLYCERIN; WATER

Easy Care First Aid AfterBurn Cream

Active Ingredients

Benzalkonium Chloride 0.13%
Lidocaine HCL 0.5%

Purpose

First Aid Antiseptic

Topical Analgesic

Uses

- temporary relief of pain associated with minor burns
- helps protect against harmful bacteria in minor burns

Warnings

For external use only.

Do not use

- in the eyes
- in large quantities
- on animal bites, serious burns, deep puncture wounds, raw surfaces, or blistered areas
- for more than one week unless directed to do so by a doctor

Stop use and ask a doctor if

- condition worsens
- if symptoms persist for more than 7 days or clears up and occurs again within a few days

Keep out of Reach of Children

If swallowed, get medical help or contact a Poison Control Center right away.

Directions

- adults and children 2 years of age and older: clean the affected area; apply a small amount to the area 1-3 times daily; may be covered with a sterile bandage (let dry first).
- children under 2 years of age: consult a doctor

Inactive Ingredients

glycerin monostearate, glycerol, purified water, sodium dodecyl sulfate